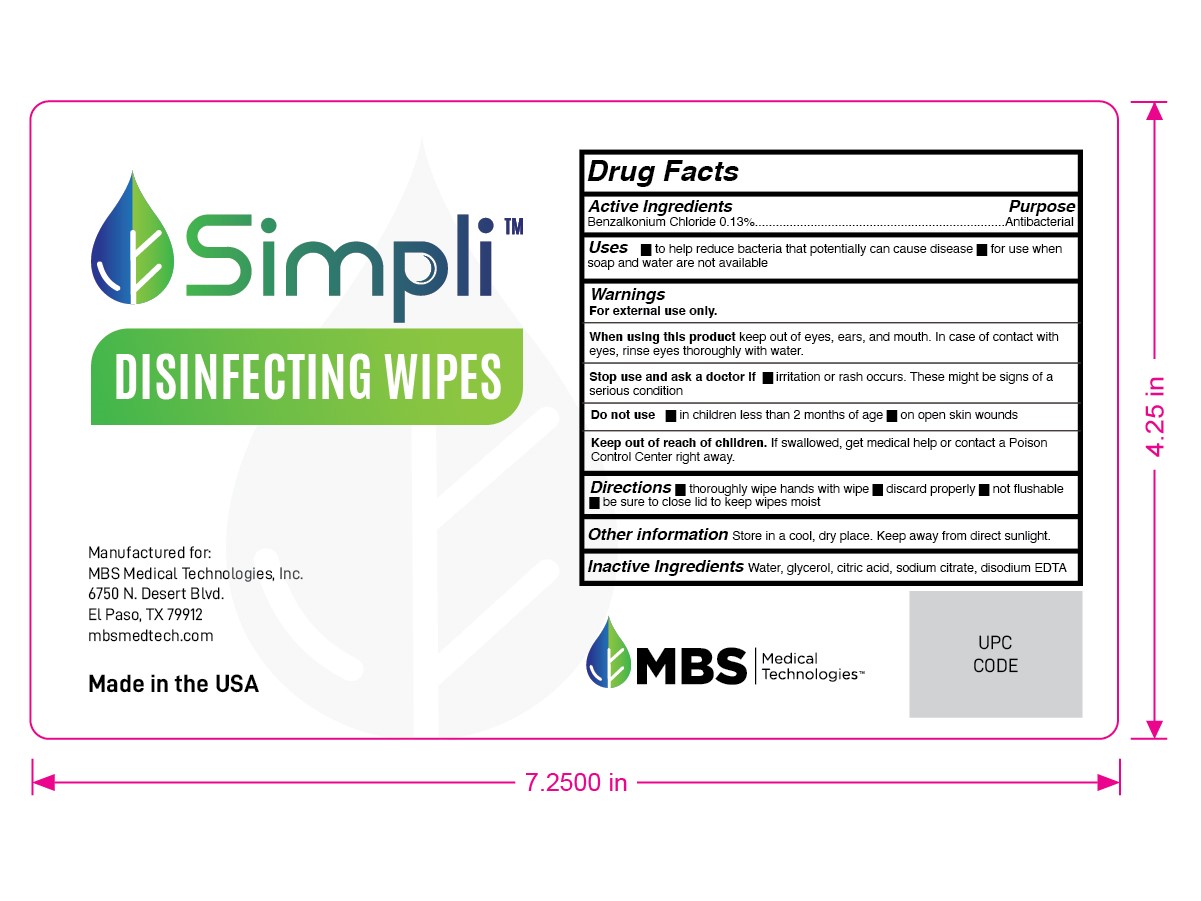 DRUG LABEL: Disinfecting Wipes
NDC: 79590-006 | Form: CLOTH
Manufacturer: MBS Medical Technologies
Category: otc | Type: HUMAN OTC DRUG LABEL
Date: 20201020

ACTIVE INGREDIENTS: BENZALKONIUM CHLORIDE 0.13 g/100 g
INACTIVE INGREDIENTS: WATER; EDETATE DISODIUM; GLYCERIN; SODIUM CITRATE; ANHYDROUS CITRIC ACID

MBS MedTech Disinfecting Wipes 0.13% Benzalkonium Chloride

Active Ingredient

Benzalkonium Chloride 0.13%

Purpose

Antibacterial

USE

For Hand Sanitizing to help reduce bacteria that potentially can cause disease

Warning

Keep out of reach of children
■Children under 6 years of age use only under adult supervision

Directions

■Wipe hands thoroughly, let skin dry and discard
■Not recommended for infants less that 2 months of age

■Not flushable

Inactive ingredients

Water, glycerol, citric acid, sodium citrate, disodium EDTA.